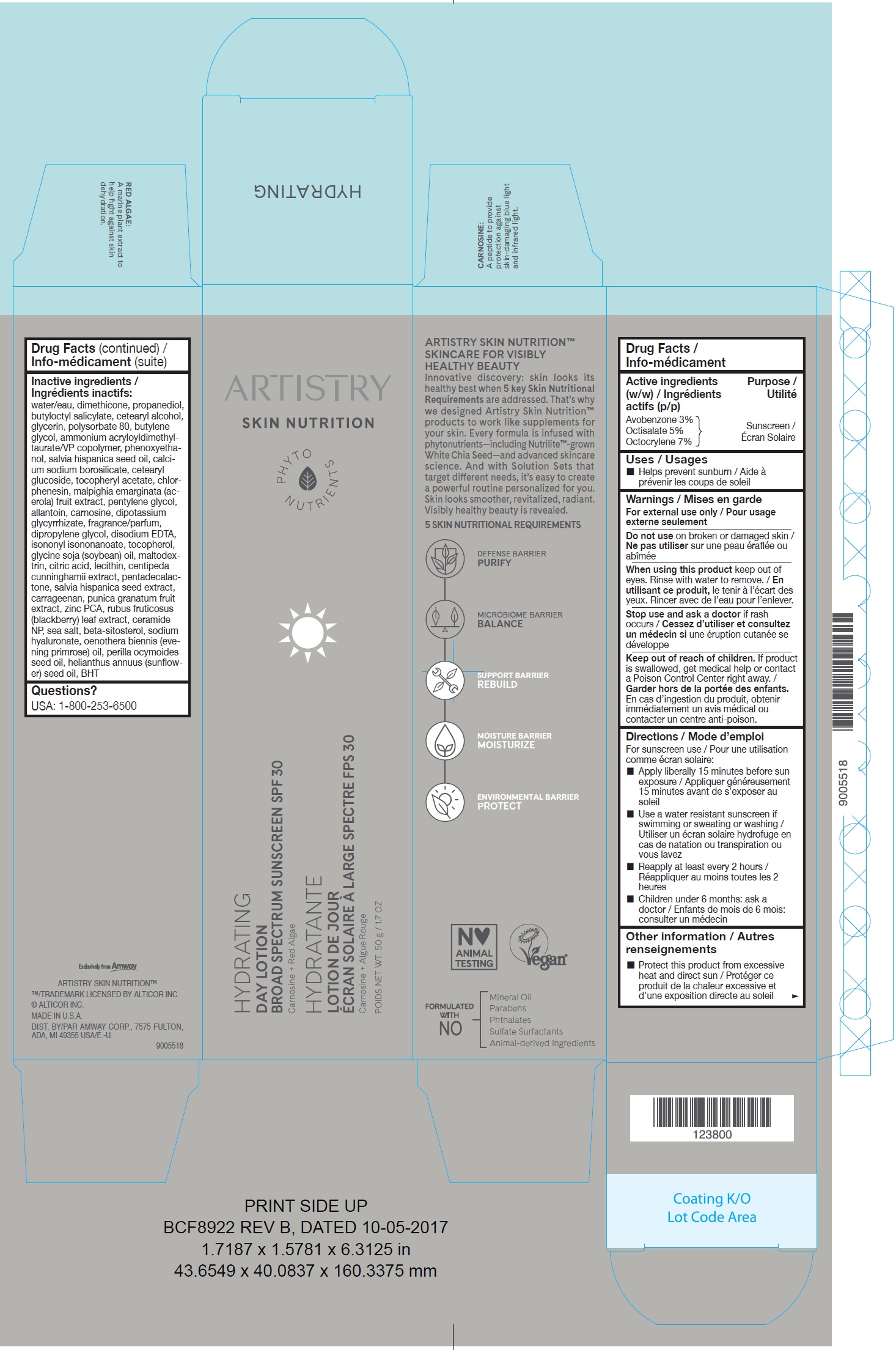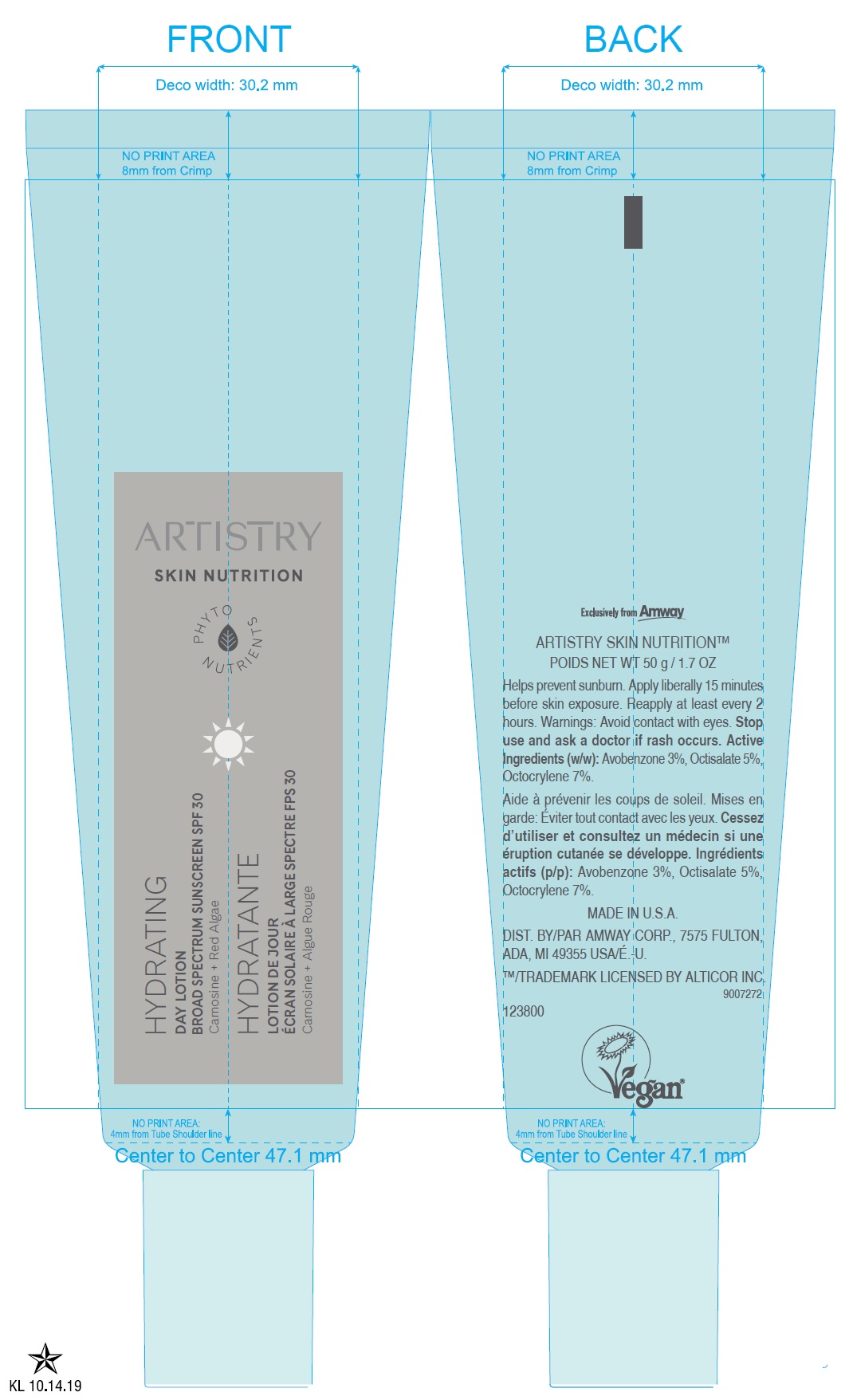 DRUG LABEL: Artistry Skin Nutrition HYDRATING Day
NDC: 10056-041 | Form: LOTION
Manufacturer: Access Business Group LLC
Category: otc | Type: HUMAN OTC DRUG LABEL
Date: 20231021

ACTIVE INGREDIENTS: AVOBENZONE 30 mg/1 g; OCTISALATE 50 mg/1 g; OCTOCRYLENE 70 mg/1 g
INACTIVE INGREDIENTS: WATER; DIMETHICONE; PROPANEDIOL; BUTYLOCTYL SALICYLATE; CETOSTEARYL ALCOHOL; GLYCERIN; POLYSORBATE 80; BUTYLENE GLYCOL; AMMONIUM ACRYLOYLDIMETHYLTAURATE/VP COPOLYMER; PHENOXYETHANOL; CHIA SEED OIL; CETEARYL GLUCOSIDE; .ALPHA.-TOCOPHEROL ACETATE; CHLORPHENESIN; ACEROLA; PENTYLENE GLYCOL; ALLANTOIN; CARNOSINE; GLYCYRRHIZINATE DIPOTASSIUM; DIPROPYLENE GLYCOL; EDETATE DISODIUM ANHYDROUS; ISONONYL ISONONANOATE; TOCOPHEROL; SOYBEAN OIL; MALTODEXTRIN; CITRIC ACID MONOHYDRATE; PENTADECALACTONE; CARRAGEENAN; POMEGRANATE; ZINC PIDOLATE; RUBUS FRUTICOSUS LEAF; CERAMIDE NP; SEA SALT; .BETA.-SITOSTEROL; HYALURONATE SODIUM; EVENING PRIMROSE OIL; PERILLA FRUTESCENS SEED OIL; SUNFLOWER OIL; BUTYLATED HYDROXYTOLUENE

Artistry Skin Nutrition HYDRATING Day Lotion

Active ingredients (w/w)

Avobenzone 3% Octisalate 5% Octocrylene 7%

Purpose

Sunscreen

Uses

Helps prevent sunburn

Warnings

For external use only

Do not use

on broken or damaged skin

When using this product

keep out of eyes. Rinse with water to remove.

Stop use and ask a doctor

if rash occurs

Keep out of reach of children.

If product is swallowed, get medical help or contact a Poison Control Center right away.

Directions

For sunscreen use

- Apply liberally 15 minutes before sun exposure
- Use a water resistant sunscreen if swimming or sweating or washing
- Reapply at least every 2 hours
- Children under 6 months: ask a doctor

Other information

- Protect this product from excessive heat and direct sun

Inactive ingredients

water, dimethicone, propanediol, butyloctyl salicylate, cetearyl alcohol, glycerin, polysorbate 80, butylene glycol, ammonium acryloyldimethyltaurate/ VP copolymer, phenoxyethanol, salvia hispanica seed oil, calcium sodium borosilicate, cetearyl glucoside, tocopheryl acetate, chlorphenesin, malpighia emarginata (acerola) fruit extract, pentylene glycol, allantoin, carnosine, dipotassium glycyrrhizate, fragrance/parfum, dipropylene glycol, disodium EDTA, isononyl isononanoate, , tocopherol, glycine soja (soybean) oil, maltodextrin, citric acid, lecithin, centipeda cunninghamii extract, pentadecalactone, salvia hispanica seed extract, carrageenan, punica granatum fruit extract, zinc PCA, rubus fruticosus (blackberry) leaf extract, ceramide NP, sea salt, beta-sitosterol, sodium hyaluronate, oenothera biennis (evening primrose) oil, perilla ocymoides seed oil, helianthus annuus (sunflower) seed oil, BHT

Questions?

USA: 1-800-253-6500